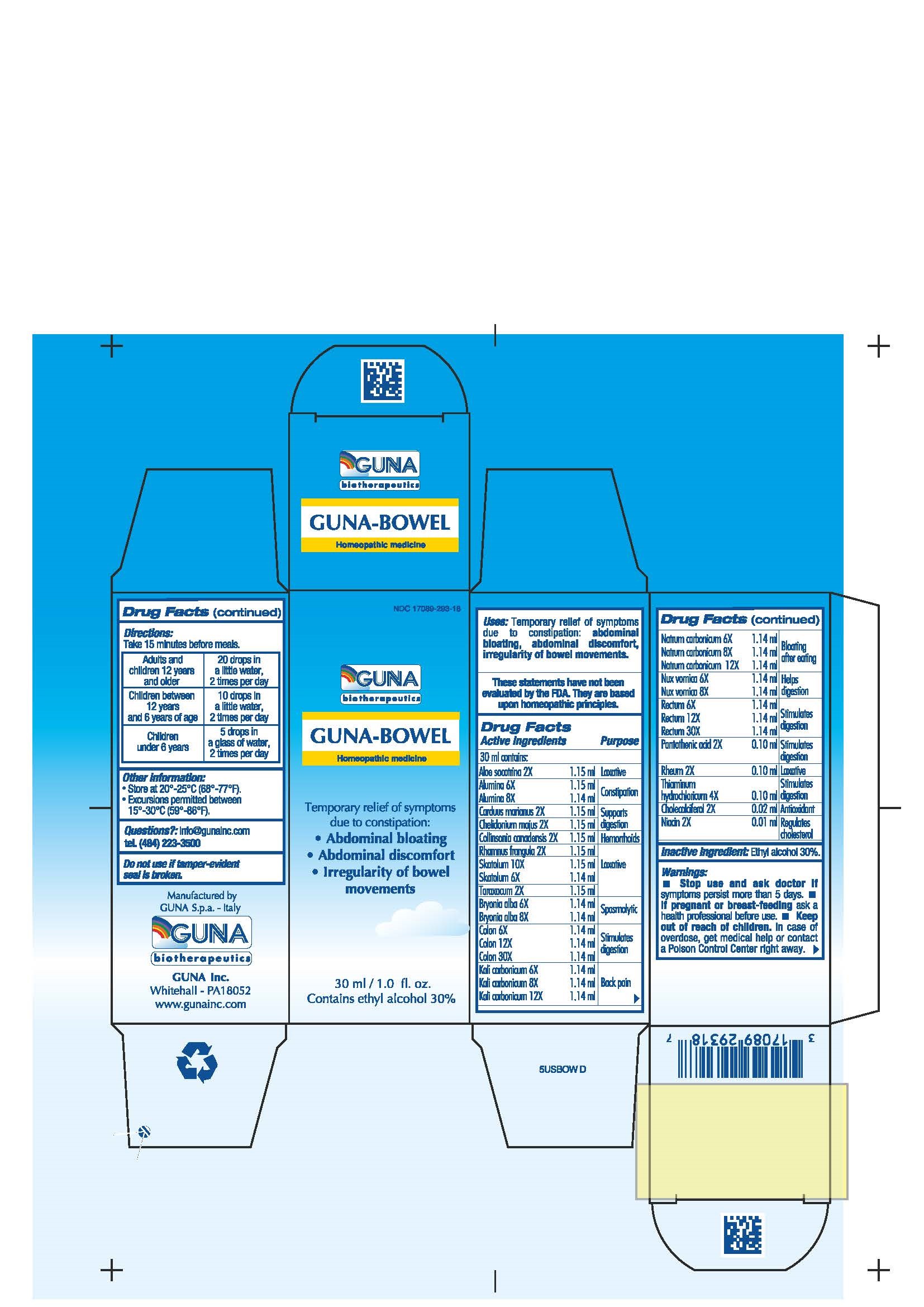 DRUG LABEL: GUNA-BOWEL
NDC: 17089-293 | Form: SOLUTION/ DROPS
Manufacturer: Guna spa
Category: homeopathic | Type: HUMAN OTC DRUG LABEL
Date: 20221114

ACTIVE INGREDIENTS: ALOE 2 [hp_X]/30 mL; ALUMINUM OXIDE 6 [hp_X]/30 mL; BRYONIA ALBA ROOT 6 [hp_X]/30 mL; SILYBUM MARIANUM SEED 2 [hp_X]/30 mL; CHELIDONIUM MAJUS 2 [hp_X]/30 mL; CHOLECALCIFEROL 2 [hp_X]/30 mL; COLLINSONIA 2 [hp_X]/30 mL; SUS SCROFA COLON 12 [hp_X]/30 mL; POTASSIUM CARBONATE 6 [hp_X]/30 mL; SODIUM CARBONATE 6 [hp_X]/30 mL; NIACIN 2 [hp_X]/30 mL; STRYCHNOS NUX-VOMICA SEED 6 [hp_X]/30 mL; PANTOTHENIC ACID 2 [hp_X]/30 mL; SUS SCROFA RECTUM 12 [hp_X]/30 mL; FRANGULA ALNUS BARK 2 [hp_X]/30 mL; RHUBARB 2 [hp_X]/30 mL; SKATOLE 10 [hp_X]/30 mL; TARAXACUM OFFICINALE 2 [hp_X]/30 mL; THIAMINE 4 [hp_X]/30 mL
INACTIVE INGREDIENTS: ALCOHOL 9 mL/30 mL

GUNA-BOWEL

ACTIVE INGREDIENTS/PURPOSE

ALOE SOCOTRINA 2X LAXATIVE
ALUMINA 6X 8X CONSTIPATION
BRYONIA ALBA 6X 8X SPASMOLYTIC
CARDUUS MARIANUS 2X SUPPORTS DIGESTION
CHELIDONIUM MAJUS 2X SUPPORTS DIGESTION
CHOLECALCIFEROL 2X ANTIOXIDANT
COLLINSONIA CANADENSIS 2X HEMORRHOIDS
COLON 6X 12X 30X STIMULATES DIGESTION
KALI CARBONICUM 6X 8X 12X BACK PAIN
NATRUM CARBONICUM 6X 8X 12X BLOATING AFTER EATING
NIACIN 2X REGULATES CHOLESTEROL
NUX VOMICA 6X 8X HELPS DIGESTION
PANTOTHENIC ACID 2X STIMULATES DIGESTION
RECTUM 6X 12X 30X STIMULATES DIGESTION
RHAMNUS FRANGULA 2X LAXATIVE
RHEUM 2X LAXATIVE
SKATOLUM 6X 10X LAXATIVE
TARAXACUM 2X LAXATIVE
THIAMINUM HYDROCHLORICUM 4X STIMULATES DIGESTION

USES

Temporary relief of symptoms due to constipation:

- Abdominal bloating
- Abdominal discomfort
- Irregularity of bowel movements

WARNINGS

- Stop use and ask doctor if symptoms persist more than 5 days.
- If pregnant or breast-feeding ask a health professional before use.
- Keep out of reach of children. In case of overdose, get medical help or contact a Poison Control Center right away.
- Contains ethyl alcohol 30%

PREGNANCY

If pregnant or breast-feeding ask a doctor before use

WARNINGS

Keep out of reach of children

DIRECTIONS

Adults and children 12 years and older 20 drops in a little water, 2 times per day
Children between 12 years and 6 years of age 10 drops in a little water, 2 times per day
Children under 6 years 5 drops in a glass of water, 2 times per day

QUESTIONS

Questions?: info@gunainc.com, tel. (484) 223-3500

Inactive ingredient: Ethyl alcohol

INDICATIONS AND USAGE

Take 15 minutes before meals